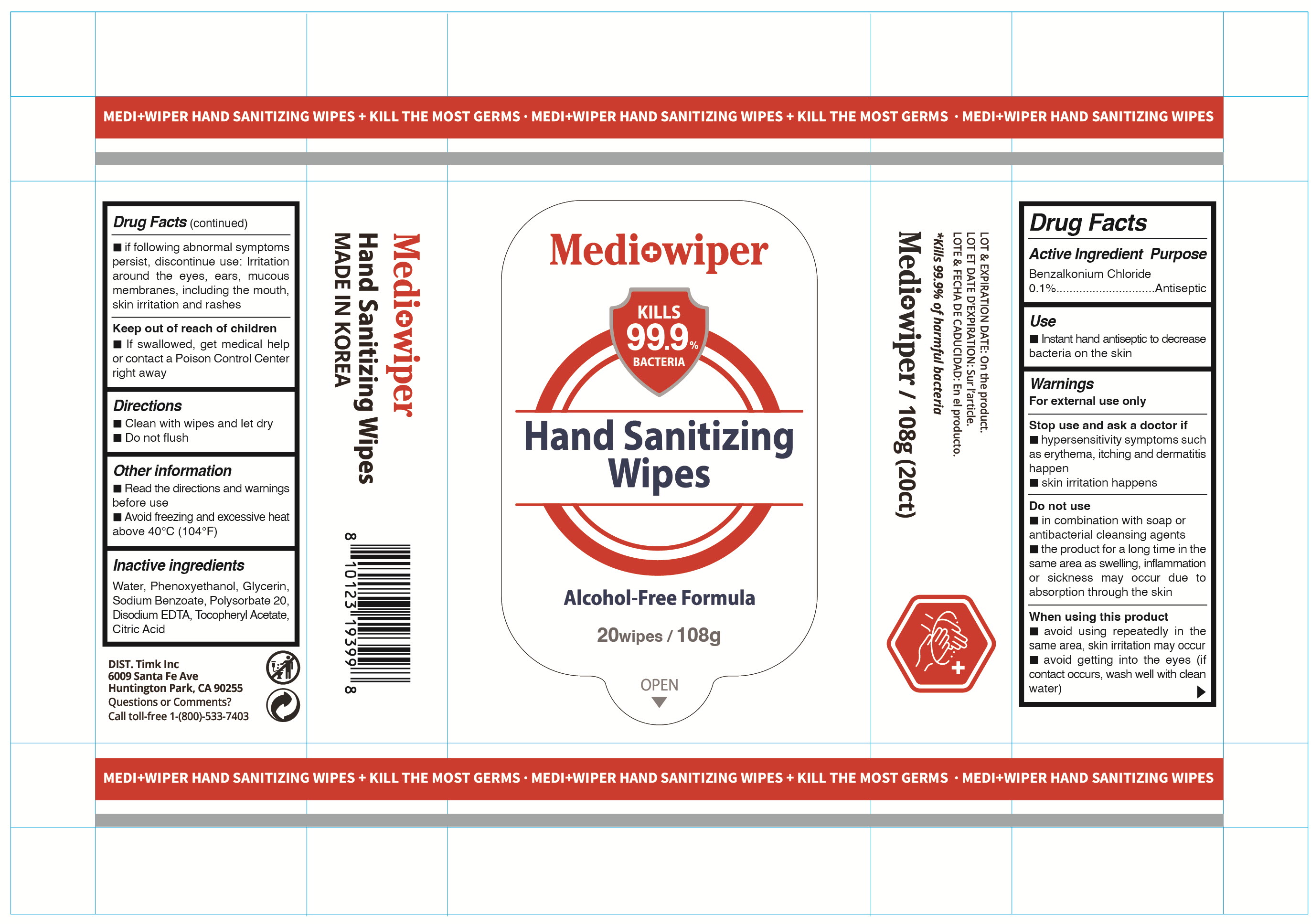 DRUG LABEL: Medi wiper Hand Sanitizing Wipes
NDC: 83930-010 | Form: LIQUID
Manufacturer: Timk Inc.
Category: otc | Type: HUMAN OTC DRUG LABEL
Date: 20240922

ACTIVE INGREDIENTS: BENZALKONIUM CHLORIDE 0.1 g/100 g
INACTIVE INGREDIENTS: WATER; POLYSORBATE 20; PHENOXYETHANOL; GLYCERIN; SODIUM BENZOATE; EDETATE DISODIUM ANHYDROUS; .ALPHA.-TOCOPHEROL ACETATE; CITRIC ACID MONOHYDRATE

Active Ingredient

Benzalkonium Chloride 0.1%

Inactive ingredients

Water, Phenoxyethanol, Glycerin, Sodium Benzoate, Polysorbate 20, Disodium EDTA, Tocopheryl Acetate, Citric Acid

Purpose

Antiseptic

Warnings

For external use only

------------------------------------------------------------------------------

Stop use and ask a doctor if
■ hypersensitivity symptoms such as erythema, itching and dermatitis happen
■ skin irritation happens

------------------------------------------------------------------------------

Do not use
■ in combination with soap or antibacterial cleansing agents
■ the product for a long time in the same area as swelling, inflammation or sickness may occur due to absorption through the skin

------------------------------------------------------------------------------

When using this product
■ avoid using repeatedly in the same area, skin irritation may occur
■ avoid getting into the eyes (if contact occurs, wash well with clean water)
■ if following abnormal symptoms persist, discontinue use: Irritation around the eyes, ears, mucous membranes, including the mouth, skin irritation and rashes

------------------------------------------------------------------------------

Keep out of reach of children
■ If swallowed, get medical help or contact a Poison Control Center right away

Keep out of reach of children

■ If swallowed, get medical help or contact a Poison Control Center right away

Use

■ Instant hand antiseptic to decrease bacteria on the skin

Directions

■ Clean with wipes and let dry
■ Do not flush

Other information

■ Read the directions and warnings before use
■ Avoid freezing and excessive heat above 40°C (104°F)